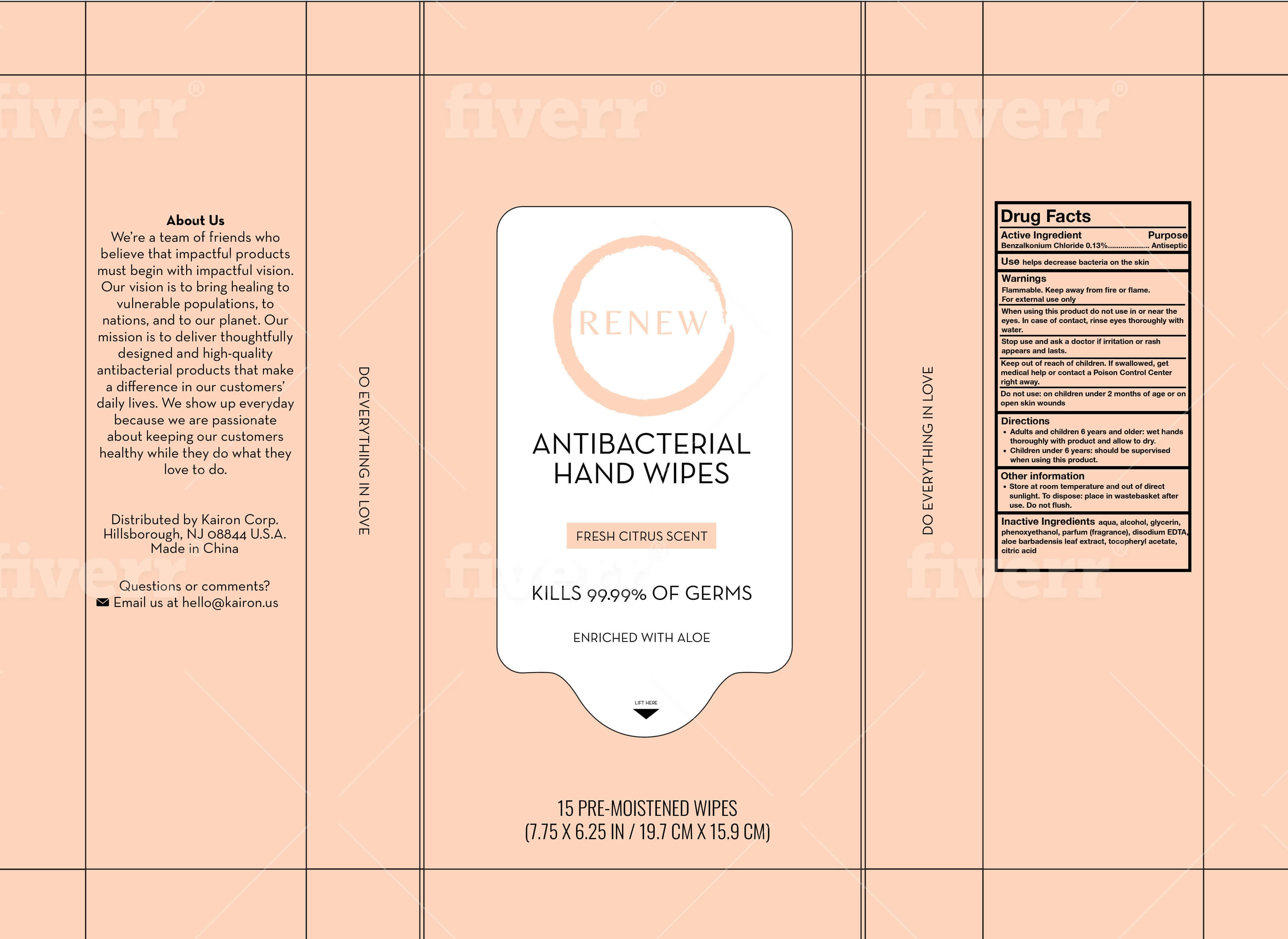 DRUG LABEL: Renew Antibacterial Hand Wipes
NDC: 78899-001 | Form: CLOTH
Manufacturer: Kairon Corp.
Category: otc | Type: HUMAN OTC DRUG LABEL
Date: 20200622

ACTIVE INGREDIENTS: BENZALKONIUM CHLORIDE 0.13 g/100 g
INACTIVE INGREDIENTS: PHENOXYETHANOL 0.3 g/100 g; GLYCERIN 0.5 g/100 g; WATER; ALCOHOL 10 g/100 g; EDETATE DISODIUM ANHYDROUS 0.05 g/100 g; .ALPHA.-TOCOPHEROL ACETATE, D- 0.01 g/100 g; ALOE VERA LEAF 0.05 g/100 g; ANHYDROUS CITRIC ACID 0.01 g/100 g

Renew Antibacterial Hand Wipes

Active Ingredient

Benzalkonium Chloride 0.13% v/v. Purpose: Antiseptic

Purpose

Antiseptic

Use

helps decrease bacteria on the skin

Warnings

Flammable. Keep away from fire or flame. For external use only

When using this product do not use in or near the eyes. In case of contact, rinse eyes thoroughly with water.

Stop use and ask a doctor if if irritation or rash appears and lasts.

Keep out of reach of children. If swallowed, get medical help or contact a Poison Control Center right away.

Do not use

on children under 2 months of age or on open skin wounds

Directions

- Adults and children 6 years and older: wet hands thoroughly with product and allow to dry.
- Children under 6 years: should be supervised when using this product.

Other information

- Store at room temperature and out of direct sunlight. To dispose: place in wastebasket after use. Do not flush.

Inactive ingredients

aqua, alcohol, glycerin, phenoxyethanol, parfum (fragrance), disodium EDTA, aloe barbadensis leaf juice, tocopheryl acetate, citric acid

PACKAGE LABEL

15 PRE-MOISTENED WIPES

NDC: 78899 -001-01